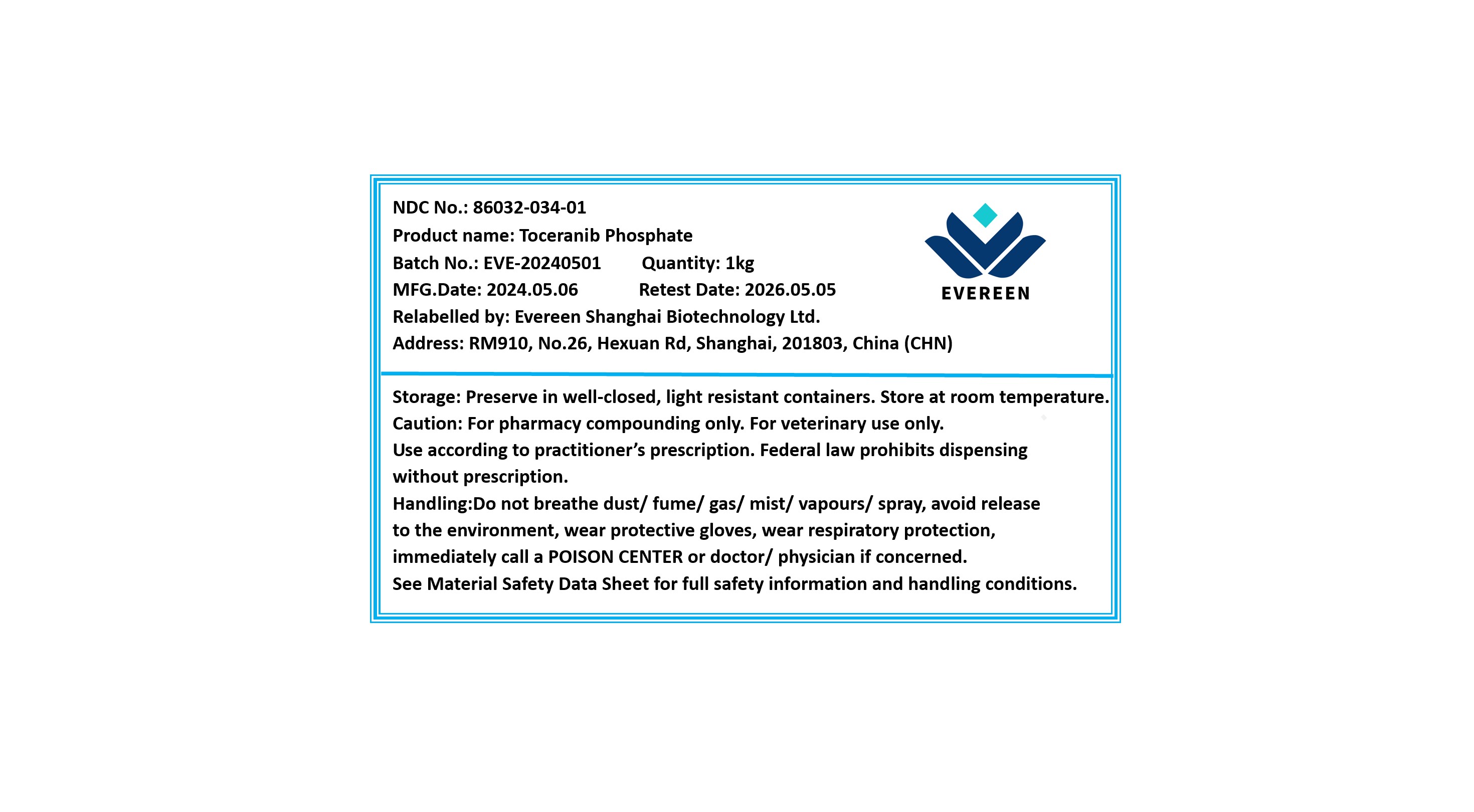 DRUG LABEL: Toceranib Phosphate
NDC: 86032-034 | Form: POWDER
Manufacturer: Evereen Shanghai Biotechnology Ltd.
Category: other | Type: BULK INGREDIENT - ANIMAL DRUG
Date: 20250312

ACTIVE INGREDIENTS: TOCERANIB PHOSPHATE 1 g/1 g

Toceranib Phosphate